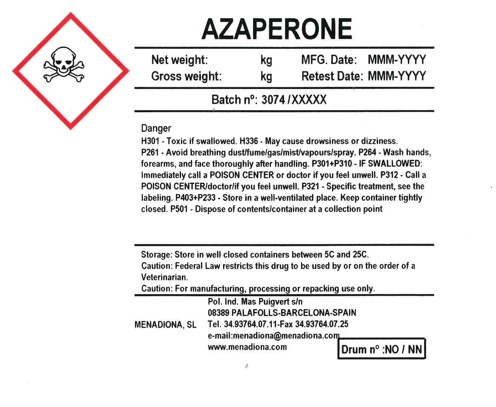 DRUG LABEL: Azaperone
NDC: 17369-074 | Form: POWDER
Manufacturer: Menadiona, S.L.
Category: other | Type: BULK INGREDIENT - ANIMAL DRUG
Date: 20220901

ACTIVE INGREDIENTS: AZAPERONE 1 kg/1 kg

PACKAGE LABEL

Azaperone